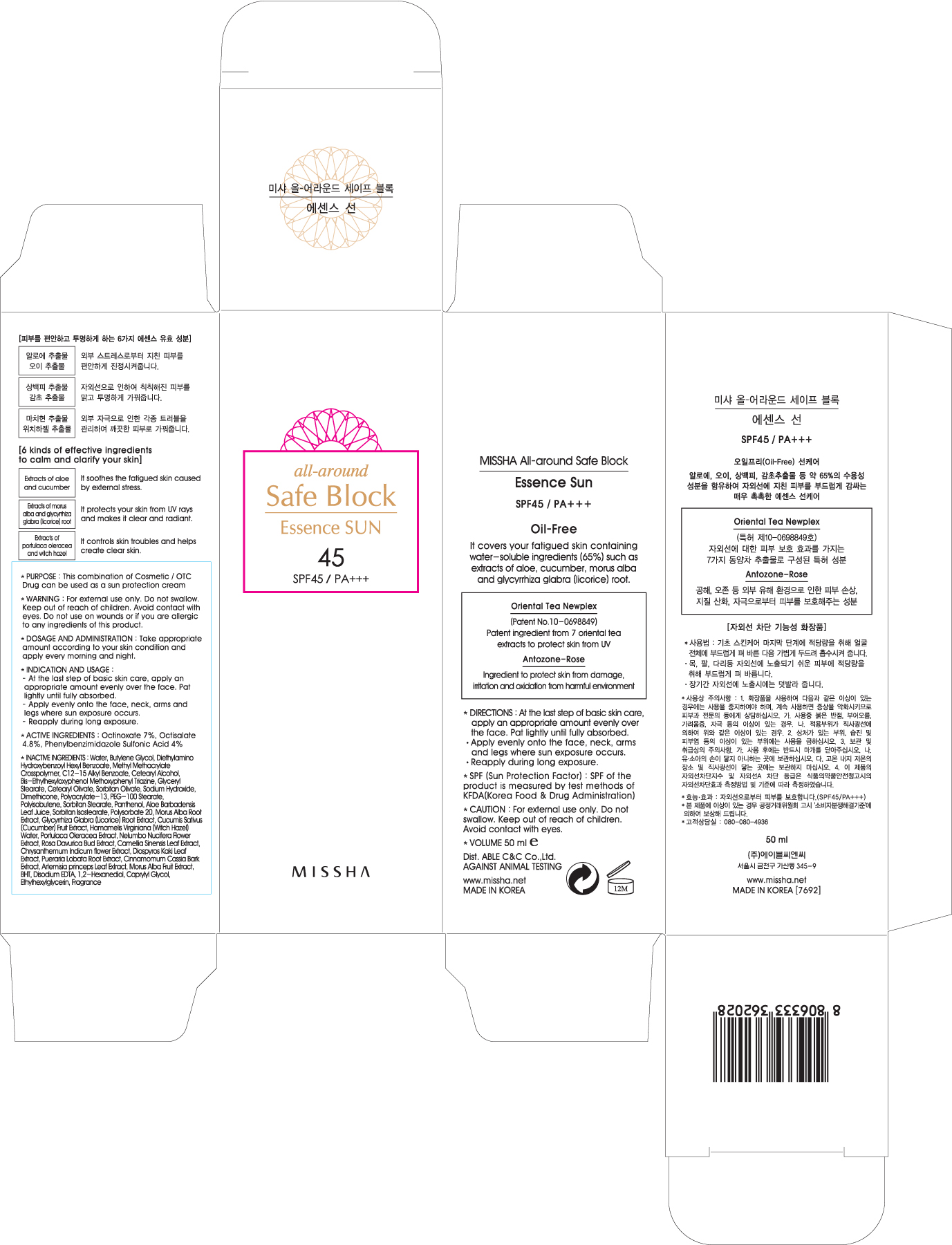 DRUG LABEL: MISSHA ALL AROUND SAFE BLOCK ESSENCE SUN
NDC: 13733-014 | Form: CREAM
Manufacturer: ABLE C&C CO., LTD.
Category: otc | Type: HUMAN OTC DRUG LABEL
Date: 20111122

ACTIVE INGREDIENTS: OCTINOXATE 3.5 mL/50 mL; OCTISALATE 2.4 mL/50 mL; ENSULIZOLE 2 mL/50 mL
INACTIVE INGREDIENTS: WATER; BUTYLENE GLYCOL; ALKYL (C12-15) BENZOATE; CETOSTEARYL ALCOHOL; GLYCERYL MONOSTEARATE; CETEARYL OLIVATE; SORBITAN OLIVATE; SODIUM HYDROXIDE; DIMETHICONE; PEG-100 STEARATE; SORBITAN MONOSTEARATE; PANTHENOL; ALOE VERA LEAF; POLYSORBATE 20; MORUS ALBA ROOT; GLYCYRRHIZA GLABRA; CUCUMBER; WITCH HAZEL; PURSLANE; NELUMBO NUCIFERA FLOWER; BANCHA TEA LEAF/TWIG; DENDRANTHEMA INDICUM FLOWER; DIOSPYROS KAKI LEAF; PUERARIA MONTANA VAR. LOBATA ROOT; CHINESE CINNAMON; ARTEMISIA PRINCEPS LEAF; BUTYLATED HYDROXYTOLUENE; EDETATE DISODIUM; 1,2-HEXANEDIOL; CAPRYLYL GLYCOL; ETHYLHEXYLGLYCERIN

Drug Facts

ACTIVE INGREDIENT

Active ingredients: Octinoxate 7%, Octisalate 4.8%, Phenylbenzimidazole Sulfonic Acid 4%

INACTIVE INGREDIENTS:
Water, Butylene Glycol, Diethylamino Hydroxybenzoyl Hexyl Benzoate, Methyl Methacrylate Crosspolymer, C12-15 Alkyl Benzoate, Cetearyl Alcohol, Bis-Ethylhexyloxyphenol Methoxyphenyl Triazine, Glyceryl Stearate, Cetearyl Olivate, Sorbitan Olivate, Sodium Hydroxide, Dimethicone, Polyacrylate-13, PEG-100 Stearate, Polyisobutene, Sorbitan Stearate, Panthenol, Aloe Barbadensis Leaf Juice, Sorbitan Isostearate, Polysorbate 20, Morus Alba Root Extract, Glycyrrhiza Glabra (Licorice) Root Extract, Cucumis Sativus (Cucumber) Fruit Extract, Hamamelis Virginiana (Witch Hazel) Water, Portulaca Oleracea Extract, Nelumbo Nucifera Flower Extract, Rosa Davurica Bud Extract, Camellia Sinensis Leaf Extract, Chrysanthemum Indicum flower Extract, Diospyros Kaki Leaf Extract, Pueraria Lobata Root Extract, Cinnamomum Cassia Bark Extract, Artemisia princeps Leaf Extract, Morus Alba Fruit Extract, BHT, Disodium EDTA, 1,2-Hexanediol, Caprylyl Glycol, Ethylhexylglycerin

PURPOSE

PURPOSE: This combination of Cosmetic / OTC Drug can be used as a sun protection cream

WARNINGS:
For external use only.
Do not swallow.
Avoid contact with eyes.
Do not use on wounds or if you are allergic to any ingredients of this product.

Keep out of reach of children:
Keep out of reach of children.

INDICATION AND USAGE:
- At the last step of basic skin care, apply an appropriate amount evenly over the face. Pat lightly until fully absorbed.
- Apply evenly onto the face, neck, arms and legs where sun exposure occurs.
- Reapply during long exposure.

DOSAGE AND ADMINISTRATION:
Take appropriate amount according to your skin condition and apply every morning and night.